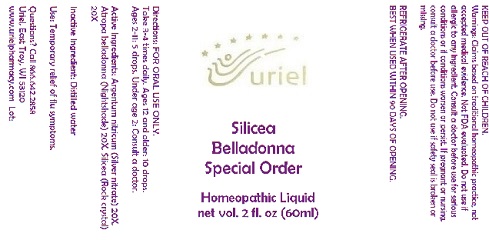 DRUG LABEL: Silicea Belladonna Special Order
NDC: 48951-8285 | Form: LIQUID
Manufacturer: Uriel Pharmacy Inc.
Category: homeopathic | Type: HUMAN OTC DRUG LABEL
Date: 20180501

ACTIVE INGREDIENTS: SILVER 20 [hp_X]/1 mL; ATROPA BELLADONNA 20 [hp_X]/1 mL; SILICON DIOXIDE 20 [hp_X]/1 mL
INACTIVE INGREDIENTS: WATER

Silicea Belladonna Special Order

INDICATIONS AND USAGE

Directions: FOR ORAL USE ONLY.

DOSAGE AND ADMINISTRATION

Take 3-4 times daily. Ages 12 and older: 10 drops. Ages 2-11: 5 drops. Under age 2: Consult a doctor.

ACTIVE INGREDIENT

Active Ingredients: Argentum nitricum (Silver nitrate) 20X, Atropa belladonna (Nightshade) 20X, Silicea (Rock crystal) 20X

Inactive Ingredient: Distilled water

PURPOSE

Use: Temporary relief of flu symptoms.

KEEP OUT OF REACH OF CHILDREN.

WARNINGS

Warnings: Claims based on traditional homeopathic practice, not accepted medical evidence. Not FDA evaluated. Do not use if allergic to any ingredient. Consult a doctor before use for serious conditions or if conditions worsen or persist. If pregnant or nursing, consult a doctor before use. Do not use if safety seal is broken or missing.

REFRIGERATE AFTER OPENING.
BEST WHEN USED WITHIN 90 DAYS OF OPENING.

QUESTIONS

Questions? Call 866.642.2858 Uriel, East Troy, WI 53120 www.urielpharmacy.com